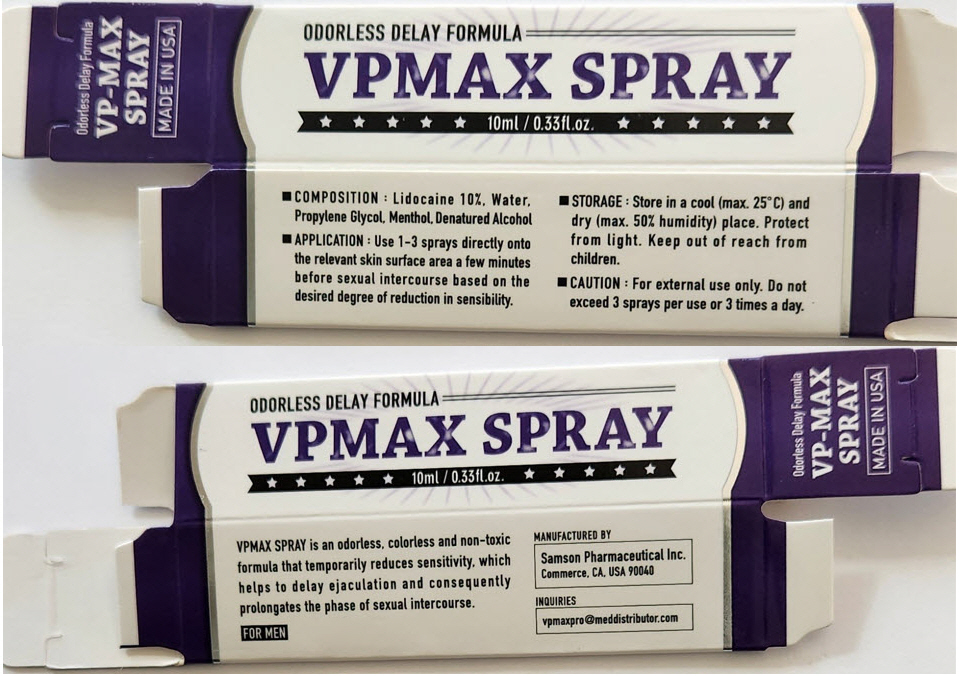 DRUG LABEL: VPMAX
NDC: 20146-5000 | Form: SPRAY
Manufacturer: SAMSON PHARMACEUTICALS INC.
Category: prescription | Type: HUMAN PRESCRIPTION DRUG LABEL
Date: 20250129

ACTIVE INGREDIENTS: LIDOCAINE 100 mg/1 mL
INACTIVE INGREDIENTS: Water; Propylene glycol; MENTHOL, UNSPECIFIED FORM

VPMAX SPRAY

PRINCIPAL DISPLAY PANEL - 10 ml Bottle Carton

ODORLESS DELAY FORMULA

VPMAX SPRAY

10ml / 0.33fl.oz.